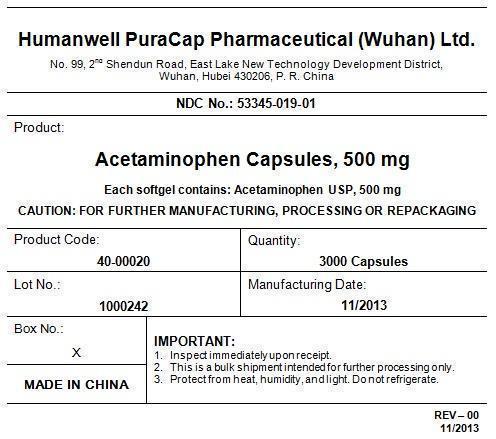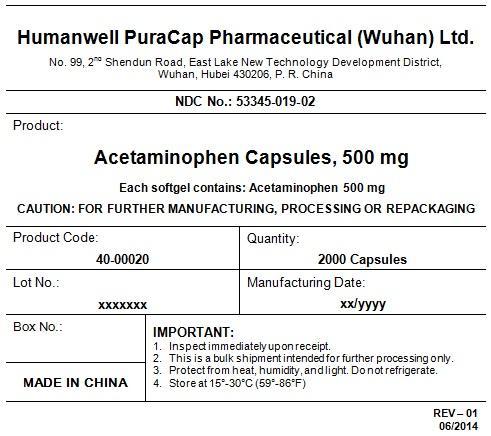 DRUG LABEL: Pain Relief Extra Strength
NDC: 53345-019 | Form: CAPSULE, LIQUID FILLED
Manufacturer: Humanwell PuraCap Pharmaceutical (Wuhan), Ltd.
Category: otc | Type: HUMAN OTC DRUG LABEL
Date: 20241125

ACTIVE INGREDIENTS: ACETAMINOPHEN 500 mg/1 1
INACTIVE INGREDIENTS: FD&C RED NO. 40; FD&C YELLOW NO. 6; GELATIN; GLYCERIN; POLYETHYLENE GLYCOL, UNSPECIFIED; POVIDONE; PROPYLENE GLYCOL; WATER; SORBITOL

Drug Facts

Active ingredient (in each capsule)

Acetaminophen 500 mg

Purpose

Pain reliever/ fever reducer

Uses

- temporarily relieves minor aches and pains due to:
  - the common cold
  - headache
  - backache
  - minor pain of arthritis
  - toothache
  - muscular aches
  - premenstrual and menstrual cramps
- temporarily reduces fever

Warnings

Liver warning:This product contains acetaminophen. The maximum daily dose of this product is 6 softgels (3,000 mg) in 24 hours. Severe liver damage may occur if you take

- more than 4,000 mg of acetaminophen in 24 hours
- with other drugs containing acetaminophen
- 3 or more alcoholic drinks every day while using this product

Do not use

- with any other drug containing acetaminophen (prescription or nonprescription). If you are not sure whether a drug contains acetaminophen, ask a doctor or pharmacist.
- if you have ever had an allergic reaction to this product or any of its ingredients

Ask a doctor before use if the user hasliver disease.

Ask a doctor or pharmacist before use if you aretaking the blood thinning drug warfarin.

Stop use and ask a doctor if

- pain gets worse or lasts more than 10 days
- fever gets worse or lasts more than 3 days
- new symptoms occur
- redness or swelling is present

These could be signs of a serious condition.

PREGNANCY OR BREAST FEEDING

If pregnant or breast-feeding,ask a health professional before use.

Keep out of reach of children.

Overdose warning

In case of overdose, get medical help or contact a Poison Control Center right away (1-800-222-1222). Quick medical attention is critical for adults as well as for children even if you do not notice any signs or symptoms.

Directions

- Do not take more than directed (see Overdose warning)

Adults and children 12 years of age and over | - take 2 softgels every 4 to 6 hours while symptoms last - do not take more than 6 softgels in 24 hours unless directed by a doctor - do not take more than 10 days unless diredted by doctor
Children 12 years of age | ask a doctor

Other information

- store at room temperature 15°-30°C (59°-86°F)

Inactive ingredients

FD&C red #40, FD&C yellow #6, gelatin, glycerin, polyethylene glycol, povidone, propylene glycol, purified water, sorbitol special and white edible ink

Manufactured by:
Humanwell PuraCap Pharmaceutical (Wuhan) Ltd.
Wuhan, Hubei
430206, China

ACETAMINOPHEN CAPSULES, 500 mg

Quantity : 3000 Capsules
NDC. No : 53345-019-01

IMP ORTANT:

Inspect immediate upon receipt.
This is a bulk shipment intended for further processing only.
Protect from heat, humidity, and light. Do not refrigerate.

CAUTION : "FOR FURTHER MANUFACTURING, PROCESSING OR REPACKING"

PRINCIPAL DISPLAY PANEL - Shipping Label

ACETAMINOPHEN CAPSULES, 500 mg

Quantity : 3000 Capsules
NDC. No : 53345-019-01

IMPORTANT:

Inspect immediate upon receipt.
This is a bulk shipment intended for further processing only.
Protect from heat, humidity, and light. Do not refrigerate.

CAUTION : "FOR FURTHER MANUFACTURING, PROCESSING OR REPACKING"